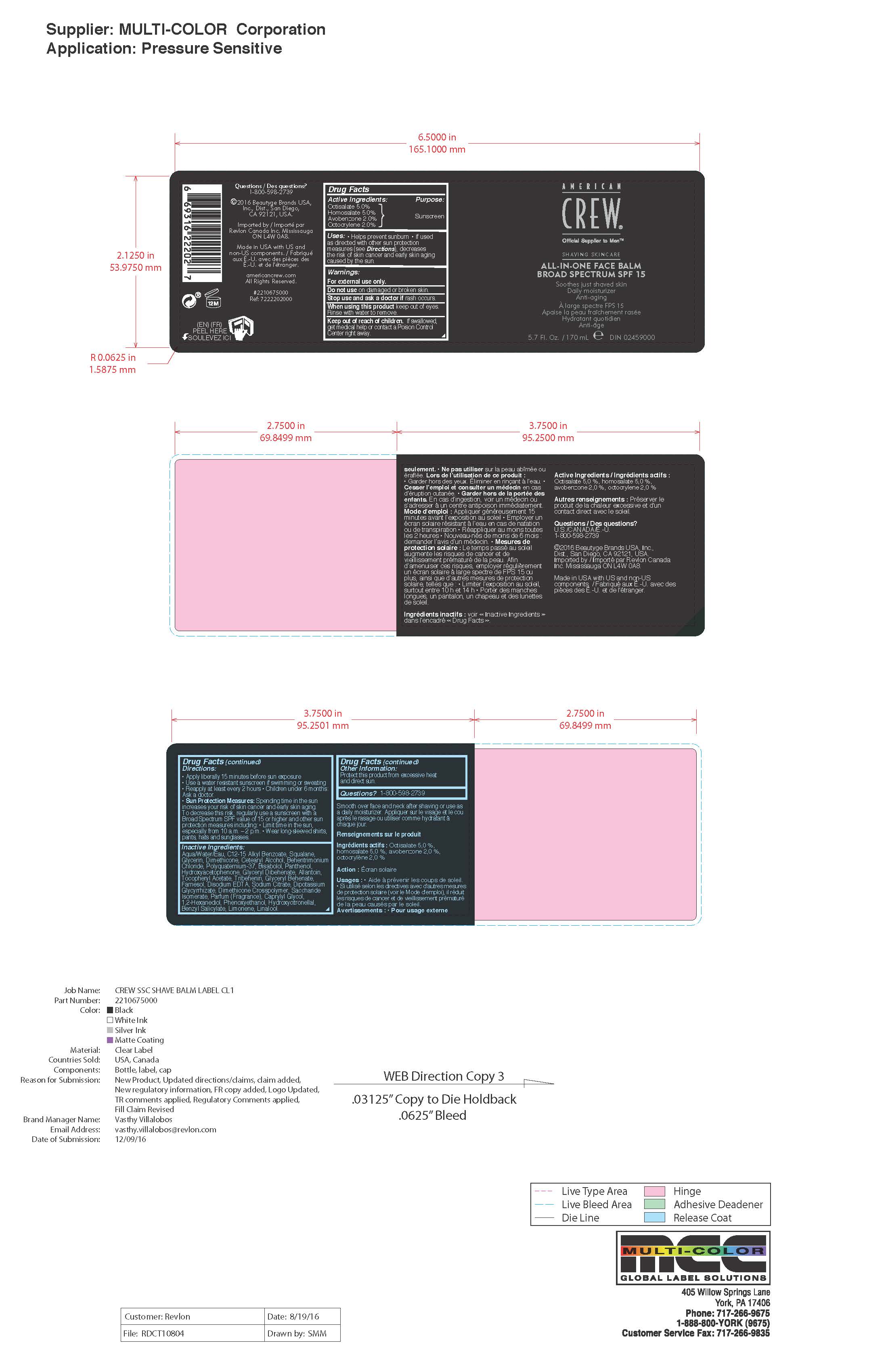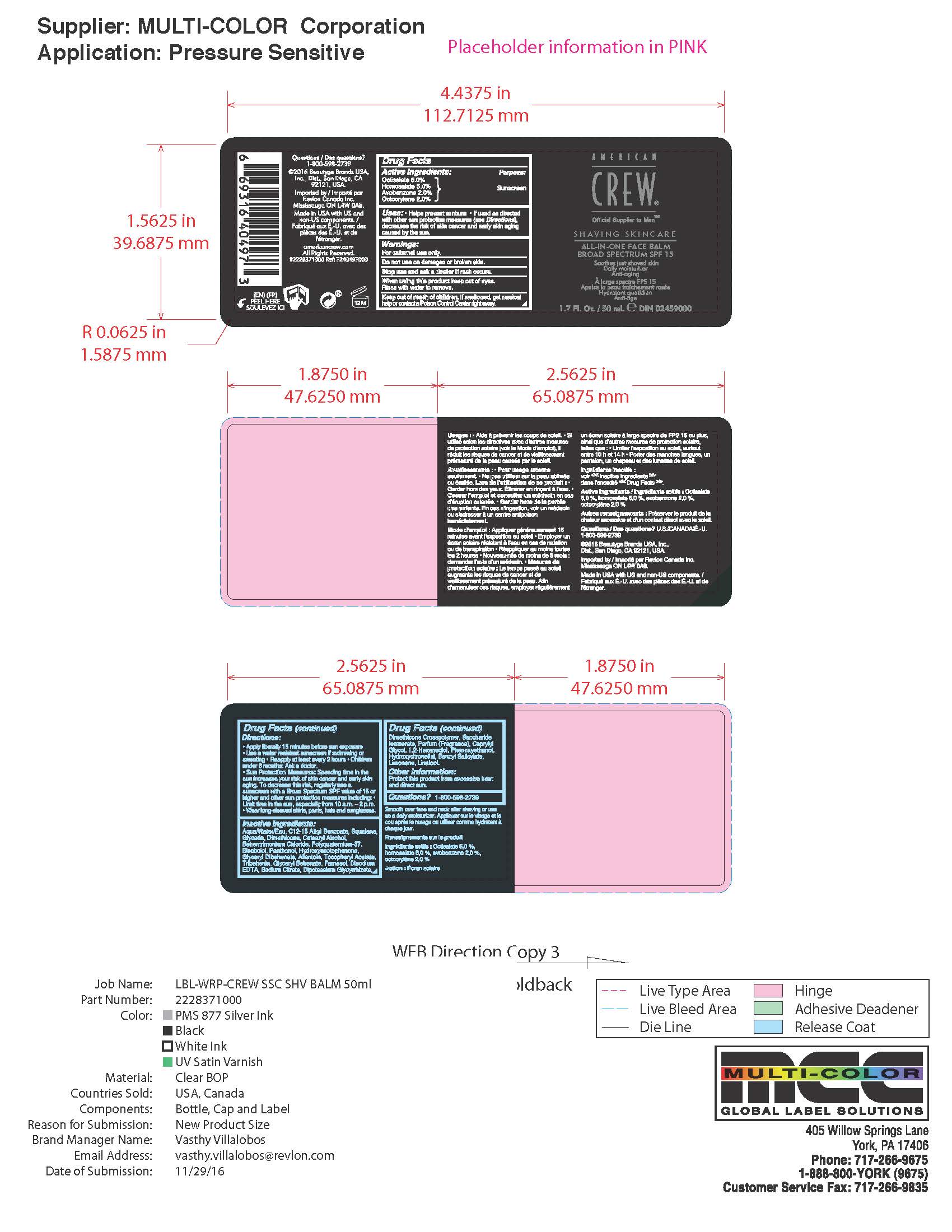 DRUG LABEL: American Crew All In One Face Balm Broad Spectrum SPF 15
NDC: 10967-651 | Form: LIQUID
Manufacturer: Revlon Consumer Products Corp
Category: otc | Type: HUMAN OTC DRUG LABEL
Date: 20241230

ACTIVE INGREDIENTS: OCTISALATE 5 mg/1 mL; HOMOSALATE 5 mg/1 mL; AVOBENZONE 2 mg/1 mL; OCTOCRYLENE 2 mg/1 mL
INACTIVE INGREDIENTS: ALKYL (C12-15) BENZOATE; SQUALANE; GLYCERIN; DIMETHICONE; CETOSTEARYL ALCOHOL; BEHENTRIMONIUM CHLORIDE; POLYQUATERNIUM-37 (10000 MPA.S); .ALPHA.-BISABOLOL, (+/-)-; DEXPANTHENOL; 4-HYDROXY ACETOPHENONE; GLYCERYL DIBEHENATE; ALLANTOIN; CAPRYLYL GLYCOL; 1,2-HEXANEDIOL; .ALPHA.-TOCOPHEROL ACETATE; TRIBEHENIN; FARNESOL; EDETATE DISODIUM ANHYDROUS; SODIUM CITRATE, UNSPECIFIED FORM; GLYCYRRHIZINATE DIPOTASSIUM; PHENOXYETHANOL; SACCHARIDE ISOMERATE; HYDROXYCITRONELLAL; BENZYL SALICYLATE; LIMONENE, (+)-; LINALOOL, (+/-)-; .BETA.-CITRONELLOL, (R)-; EUGENOL; GERANIOL; BENZYL BENZOATE; CITRAL; CINNAMYL ALCOHOL

American Crew All in One Face Balm

Active Ingredients

Octisalate 5.0%

Homosalate 5.0%

Avobenzone 2.0%

Octocrylene 2.0%

Purpose

Sunscreen

Uses

Helps prevent sunburn • If used
as directed with other sun protection
measures (see Directions), decreases
the risk of skin cancer and early skin aging
caused by the sun.

Warnings

•For external use only
•Do notuse on damaged or broken skin
•When using this product: Keep out of eyes. Rinse with water to remove.
•Stop use and ask a doctor if a rash occurs
•Keep out of reach of children. If product is swallowed, get medical help or contact a Poison Control center right away

Directions

•Apply liberally 15 minutes before sun exposure
•Use a water resistant sunscreen if swimming or sweating
•Reapply at least every 2 hours
•Children under 6 months: Ask a doctor.

Sun protection measures

Spending time in the sun increases your risk of skin cancer and early skin aging. To decrease this risk, regularly use a sunscreen with a Broad Spectrum SPF value of 15 or higher and other sun protection measures including:
•Limit time in the sun, especially from 10 am - 2 pm
•Wear long-sleeved shirts, pants, hats and sunglasses.

Inactive Ingredients

Aqua/Water/Eau, C12-15 Alkyl Benzoate, Squalane,
Glycerin, Dimethicone, Cetearyl Alcohol, Behentrimonium
Chloride, Polyquaternium-37, Bisabolol, Panthenol,
Hydroxyacetophenone, Glyceryl Dibehenate, Allantoin,
Tocopheryl Acetate, Tribehenin, Glyceryl Behenate,
Farnesol, Disodium EDTA, Sodium Citrate, Dipotassium
Glycyrrhizate, Dimethicone Crosspolymer, Saccharide
Isomerate, Parfum (Fragrance), Caprylyl Glycol,
1,2-Hexanediol, Phenoxyethanol, Hydroxycitronellal,

Questions?

1-800-598-2739

•Keep out of reach of children. If product is swallowed, get medical help or contact a Poison Control center right away

DOSAGE AND ADMINISTRATION

Apply liberally 15 minutes before sun exposure

PACKAGE LABEL

American Crew All in One Face Balm

Broad Spectrum SPF 15

170mL

PACKAGE LABEL

American Crew All in One Face Balm

Broad Spectrum SPF 15

50mL